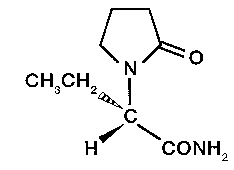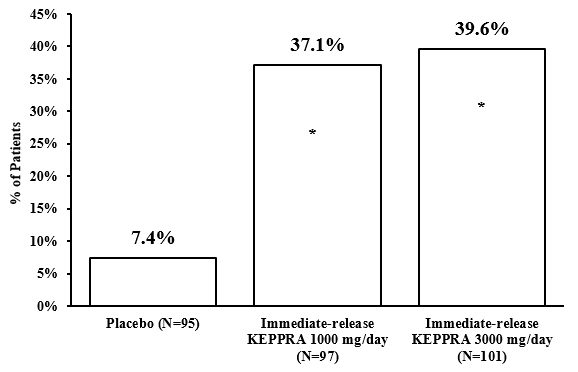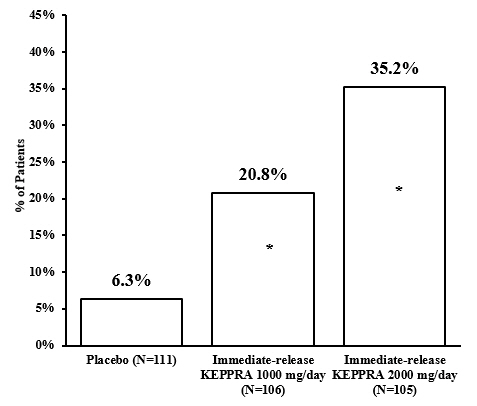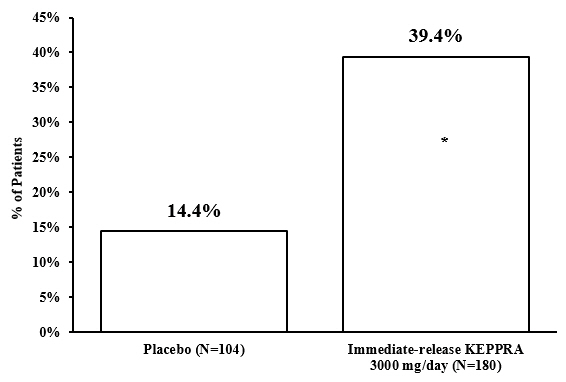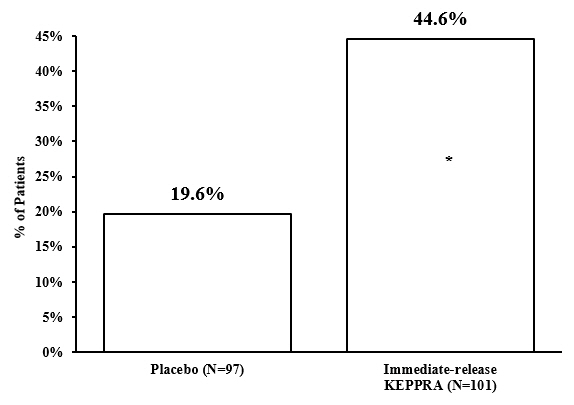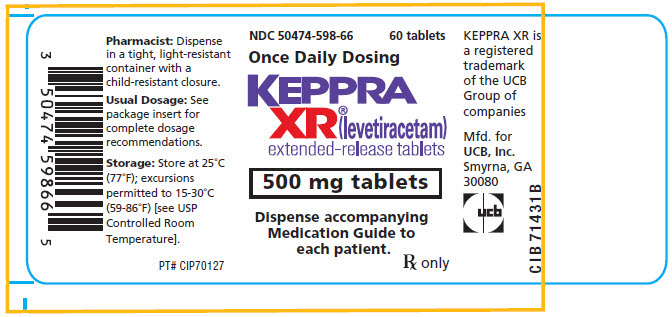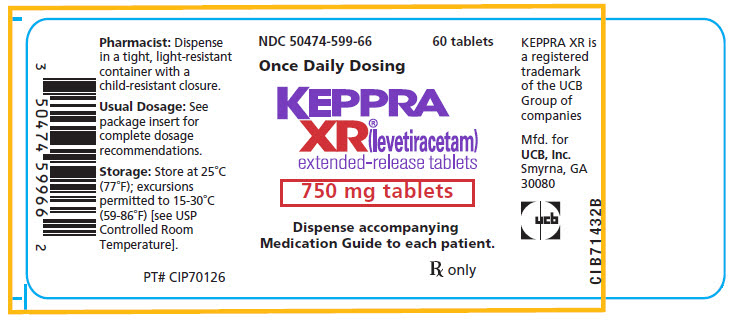 DRUG LABEL: Keppra 

NDC: 50474-599 | Form: TABLET, FILM COATED, EXTENDED RELEASE
Manufacturer: UCB, Inc.
Category: prescription | Type: HUMAN PRESCRIPTION DRUG LABEL
Date: 20250624

ACTIVE INGREDIENTS: LEVETIRACETAM 750 mg/1 1
INACTIVE INGREDIENTS: SILICON DIOXIDE; HYPROMELLOSE, UNSPECIFIED; MAGNESIUM STEARATE; POLYETHYLENE GLYCOL 6000; POLYVINYL ALCOHOL, UNSPECIFIED; POLYETHYLENE GLYCOL 3350; TALC; SHELLAC; FD&C RED NO. 40; BUTYL ALCOHOL; PROPYLENE GLYCOL; ALCOHOL; METHYL ALCOHOL

HIGHLIGHTS OF PRESCRIBING INFORMATION

These highlights do not include all the information needed to use KEPPRA XR®safely and effectively. See full prescribing information for KEPPRA XR.
KEPPRA XR (levetiracetam) extended-release tablets, for oral use
Initial U.S. Approval: 1999

RECENT MAJOR CHANGES

Warnings and Precautions (5.6) | 3/2024

1 INDICATIONS AND USAGE

KEPPRA XR is indicated for the treatment of partial-onset seizures in patients 12 years of age and older (1)

2 DOSAGE AND ADMINISTRATION

Initiate treatment with a dose of 1000 mg once daily; increase by 1000 mg every 2 weeks to a maximum recommended dose of 3000 mg once daily (2)

See full prescribing information for use in patients with impaired renal function (2.1)

3 DOSAGE FORMS AND STRENGTHS

- 500 mg white, film-coated extended-release tablet (3)
- 750 mg white, film-coated extended-release tablet (3)

4 CONTRAINDICATIONS

Known hypersensitivity to levetiracetam; angioedema and anaphylaxis have occurred (4, 5.4)

5 WARNINGS AND PRECAUTIONS

- Behavioral abnormalities including psychotic symptoms, suicidal ideation, irritability, and aggressive behavior have been observed; monitor patients for psychiatric signs and symptoms (5.1)
- Suicidal Behavior and Ideation: Monitor patients for new or worsening depression, suicidal thoughts/behavior, and/or unusual changes in mood or behavior (5.2)
- Monitor for somnolence and fatigue and advise patients not to drive or operate machinery until they have gained sufficient experience on KEPPRA XR (5.3)
- Serious Dermatological Reactions: Discontinue KEPPRA at the first sign of rash unless clearly not drug related (5.5)
- Drug Reaction with Eosinophilia and Systemic Symptoms (DRESS)/Multiorgan Hypersensitivity: Discontinue if no alternative etiology (5.6)
- Coordination Difficulties: Monitor for ataxia, abnormal gait, and incoordination. Advise patients to not drive or operate machinery until they have gained experience on KEPPRA (5.7)
- Withdrawal Seizures: KEPPRA XR must be gradually withdrawn (5.8)

6 ADVERSE REACTIONS

Most common adverse reactions (incidence ≥5% more than placebo) include: somnolence and irritability (6.1)

To report SUSPECTED ADVERSE REACTIONS, contact UCB, Inc. at (844) 599-CARE (2273) or FDA at 1-800-FDA-1088 or www.fda.gov/medwatch.

8 USE IN SPECIFIC POPULATIONS

Pregnancy: Plasma levels of levetiracetam may be decreased and therefore need to be monitored closely during pregnancy. Based on animal data, may cause fetal harm (5.10, 8.1)

FULL PRESCRIBING INFORMATION

1 INDICATIONS AND USAGE

KEPPRA XR®is indicated for the treatment of partial-onset seizures in patients 12 years of age and older.

2 DOSAGE AND ADMINISTRATION

2.1 Recommended Dosing

For adults and adolescent patients, the recommended dosing for monotherapy and adjunctive therapy is the same; as outlined below.

Adults and Adolescents 12 Years of Age and Older Weighing 50 kg or More

Initiate treatment with a dose of 1000 mg once daily. The once daily dosage may be adjusted in increments of 1000 mg every 2 weeks to a maximum recommended daily dose of 3000 mg/day once daily.

Administration

KEPPRA XR is administered once daily. KEPPRA XR tablets should be swallowed whole. The tablets should not be chewed, broken, or crushed.

2.2 Dosage Adjustments in Adult Patients with Renal Impairment

KEPPRA XR dosing must be individualized according to the patient's renal function status. Recommended dosage adjustments for adults are shown in Table 1. In order to calculate the dose recommended for patients with renal impairment, creatinine clearance adjusted for body surface area must be calculated. To do this, an estimate of the patient's creatinine clearance (CLcr) in mL/min must first be calculated using the following formula:

CLcr= | [140-age (years)] × weight (kg) -------------------------------------- | (× 0.85 for female patients)
CLcr= | 72 × serum creatinine (mg/dL) | (× 0.85 for female patients)

Then CLcr is adjusted for body surface area (BSA) as follows:

CLcr (mL/min/1.73m^2)= | CLcr (mL/min) ------------------------- | × 1.73
CLcr (mL/min/1.73m^2)= | BSA subject (m^2) | × 1.73

Table 1: Dosage Adjustment Regimen for Adult Patients with Renal Impairment
Group | Creatinine Clearance (mL/min/1.73m^2) | Dosage (mg) | Frequency
Normal | > 80 | 1000 to 3000 | Every 24 hours
Mild | 50 – 80 | 1000 to 2000 | Every 24 hours
Moderate | 30 – 50 | 500 to 1500 | Every 24 hours
Severe | < 30 | 500 to 1000 | Every 24 hours

2.3 Discontinuation of KEPPRA XR

Avoid abrupt withdrawal from KEPPRA XR in order to reduce the risk of increased seizure frequency and status epilepticus [see Warnings and Precautions (5.8)].

3 DOSAGE FORMS AND STRENGTHS

KEPPRA XR tablets are white, oblong-shaped, film-coated extended-release tablets imprinted in red with "UCB 500XR" on one side and contain 500 mg levetiracetam.

KEPPRA XR tablets are white, oblong-shaped, film-coated extended-release tablets imprinted in red with "UCB 750XR" on one side and contain 750 mg levetiracetam.

4 CONTRAINDICATIONS

KEPPRA XR is contraindicated in patients with a hypersensitivity to levetiracetam .Reactions have included anaphylaxis and angioedema [see Warnings and Precautions (5.4)] .

5 WARNINGS AND PRECAUTIONS

5.1 Behavioral Abnormalities and Psychotic Symptoms

KEPPRA XR may cause behavioral abnormalities and psychotic symptoms. Patients treated with KEPPRA XR should be monitored for psychiatric signs and symptoms.

Behavioral abnormalities

KEPPRA XR Tablets

A total of 7% of KEPPRA XR-treated patients experienced non-psychotic behavioral disorders (reported as irritability and aggression) compared to 0% of placebo-treated patients. Irritability was reported in 7% of KEPPRA XR-treated patients. Aggression was reported in 1% of KEPPRA XR-treated patients.

No patient discontinued treatment or had a dose reduction as a result of these adverse reactions.

The number of patients exposed to KEPPRA XR was considerably smaller than the number of patients exposed to immediate-release KEPPRA tablets in controlled trials. Therefore, certain adverse reactions observed in the immediate-release KEPPRA controlled trials will likely occur in patients receiving KEPPRA XR.

Immediate-Release KEPPRA Tablets

A total of 13% of adult patients and 38% of pediatric patients (4 to 16 years of age) treated with immediate-release KEPPRA experienced non-psychotic behavioral symptoms (reported as aggression, agitation, anger, anxiety, apathy, depersonalization, depression, emotional lability, hostility, hyperkinesias, irritability, nervousness, neurosis, and personality disorder), compared to 6% and 19% of adult and pediatric patients on placebo. A randomized, double-blind, placebo-controlled study was performed to assess the neurocognitive and behavioral effects of immediate-release KEPPRA tablets as adjunctive therapy in pediatric patients (4 to 16 years of age). An exploratory analysis suggested a worsening in aggressive behavior in patients treated with immediate-release KEPPRA tablets in that study [see Use in Specific Populations (8.4)] .

A total of 1.7% of adult patients treated with immediate-release KEPPRA discontinued treatment due to behavioral adverse reactions, compared to 0.2% of placebo-treated patients. The treatment dose was reduced in 0.8% of adult patients treated with immediate-release KEPPRA, compared to 0.5% of placebo-treated patients. Overall, 11% of pediatric patients treated with immediate-release KEPPRA experienced behavioral symptoms associated with discontinuation or dose reduction, compared to 6.2% of placebo-treated pediatric patients.

One percent of adult patients and 2% of pediatric patients (4 to 16 years of age) treated with immediate-release KEPPRA experienced psychotic symptoms, compared to 0.2% and 2%, respectively, in adult and placebo-treated pediatric patients. In the controlled study that assessed the neurocognitive and behavioral effects of immediate-release KEPPRA in pediatric patients 4 to 16 years of age, 1.6% KEPPRA-treated patients experienced paranoia, compared to no placebo-treated patients. There were 3.1% patients treated with immediate-release KEPPRA who experienced confusional state, compared to no placebo-treated patients [see Use in Specific Populations (8.4)] .

Psychotic symptoms

Immediate-Release KEPPRA tablets

One percent of KEPPRA-treated adult patients experienced psychotic symptoms compared to 0.2% of placebo-treated patients.

Two (0.3%) KEPPRA-treated adult patients were hospitalized and their treatment was discontinued due to psychosis. Both events, reported as psychosis, developed within the first week of treatment and resolved within 1 to 2 weeks following treatment discontinuation. There was no difference between drug and placebo-treated patients in the incidence of pediatric patients who discontinued treatment due to psychotic and non-psychotic adverse reactions.

5.2 Suicidal Behavior and Ideation

Antiepileptic drugs (AEDs), including KEPPRA XR, increase the risk of suicidal thoughts or behavior in patients taking these drugs for any indication. Patients treated with any AED for any indication should be monitored for the emergence or worsening of depression, suicidal thoughts or behavior, and/or any unusual changes in mood or behavior.

Pooled analyses of 199 placebo-controlled clinical trials (mono- and adjunctive therapy) of 11 different AEDs showed that patients randomized to one of the AEDs had approximately twice the risk (adjusted Relative Risk 1.8, 95% CI:1.2, 2.7) of suicidal thinking or behavior compared to patients randomized to placebo. In these trials, which had a median treatment duration of 12 weeks, the estimated incidence rate of suicidal behavior or ideation among 27,863 AED-treated patients was 0.43%, compared to 0.24% among 16,029 placebo-treated patients, representing an increase of approximately one case of suicidal thinking or behavior for every 530 patients treated. There were four suicides in drug-treated patients in the trials and none in placebo-treated patients, but the number is too small to allow any conclusion about drug effect on suicide.

The increased risk of suicidal thoughts or behavior with AEDs was observed as early as one week after starting drug treatment with AEDs and persisted for the duration of treatment assessed. Because most trials included in the analysis did not extend beyond 24 weeks, the risk of suicidal thoughts or behavior beyond 24 weeks could not be assessed.

The risk of suicidal thoughts or behavior was generally consistent among drugs in the data analyzed. The finding of increased risk with AEDs of varying mechanisms of action and across a range of indications suggests that the risk applies to all AEDs used for any indication. The risk did not vary substantially by age (5-100 years) in the clinical trials analyzed. Table 2 shows absolute and relative risk by indication for all evaluated AEDs.

Table 2: Risk by Indication for Antiepileptic Drugs in the Pooled Analysis
Indication | Placebo Patients with Events Per 1000 Patients | Drug Patients with Events Per 1000 Patients | Relative Risk: Incidence of Events in Drug Patients/Incidence in Placebo Patients | Risk Difference: Additional Drug Patients with Events Per 1000 Patients
Epilepsy | 1.0 | 3.4 | 3.5 | 2.4
Psychiatric | 5.7 | 8.5 | 1.5 | 2.9
Other | 1.0 | 1.8 | 1.9 | 0.9
Total | 2.4 | 4.3 | 1.8 | 1.9

The relative risk for suicidal thoughts or behavior was higher in clinical trials for epilepsy than in clinical trials for psychiatric or other conditions, but the absolute risk differences were similar for the epilepsy and psychiatric indications.

Anyone considering prescribing KEPPRA XR or any other AED must balance the risk of suicidal thoughts or behavior with the risk of untreated illness. Epilepsy and many other illnesses for which AEDs are prescribed are themselves associated with morbidity and mortality and an increased risk of suicidal thoughts and behavior. Should suicidal thoughts and behavior emerge during treatment, the prescriber needs to consider whether the emergence of these symptoms in any given patient may be related to the illness being treated.

5.3 Somnolence and Fatigue

KEPPRA XR may cause somnolence and fatigue. Patients should be monitored for these signs and symptoms and advised not to drive or operate machinery until they have gained sufficient experience on KEPPRA XR to gauge whether it adversely affects their ability to drive or operate machinery.

Somnolence

KEPPRA XR Tablets

In the KEPPRA XR double-blind, controlled trial in patients experiencing partial-onset seizures, 8% of KEPPRA XR-treated patients experienced somnolence compared to 3% of placebo-treated patients.

No patient discontinued treatment or had a dose reduction as a result of these adverse reactions.

The number of patients exposed to KEPPRA XR was considerably smaller than the number of patients exposed to immediate-release KEPPRA tablets in controlled trials. Therefore, certain adverse reactions observed in the immediate-release KEPPRA controlled trials will likely occur in patients receiving KEPPRA XR.

Immediate-Release KEPPRA Tablets

In controlled trials of adult patients with epilepsy experiencing partial-onset seizures, 15% of KEPPRA-treated patients reported somnolence, compared to 8% of placebo-treated patients. There was no clear dose response up to 3000 mg/day. In a study where there was no titration, about 45% of patients receiving 4000 mg/day reported somnolence. The somnolence was considered serious in 0.3% of the KEPPRA-treated patients, compared to 0% in the placebo group. About 3% of KEPPRA-treated patients discontinued treatment due to somnolence, compared to 0.7% of placebo-treated patients. In 1.4% of KEPPRA-treated patients and in 0.9% of placebo-treated patients the dose was reduced, while 0.3% of the treated patients were hospitalized due to somnolence.

Asthenia

Immediate-Release KEPPRA Tablets

In controlled trials of adult patients with epilepsy experiencing partial-onset seizures, 15% of KEPPRA-treated patients reported asthenia, compared to 9% of placebo-treated patients. Treatment was discontinued due to asthenia in 0.8% of KEPPRA-treated patients as compared to 0.5% of placebo-treated patients. In 0.5% of KEPPRA-treated patients and in 0.2% of placebo-treated patients, the dose was reduced due to asthenia.

Somnolence and asthenia occurred most frequently within the first 4 weeks of treatment.

5.4 Anaphylaxis and Angioedema

KEPPRA XR can cause anaphylaxis or angioedema after the first dose or at any time during treatment. Signs and symptoms in cases reported in the postmarketing setting in patients treated with levetiracetam have included hypotension, hives, rash, respiratory distress, and swelling of the face, lip, mouth, eye, tongue, throat, and feet. In some reported cases, reactions were life-threatening and required emergency treatment. If a patient develops signs or symptoms of anaphylaxis or angioedema, KEPPRA XR should be discontinued and the patient should seek immediate medical attention. KEPPRA XR should be discontinued permanently if a clear alternative etiology for the reaction cannot be established [see Contraindications (4)] .

5.5 Serious Dermatological Reactions

Serious dermatological reactions, including Stevens-Johnson syndrome (SJS) and toxic epidermal necrolysis (TEN), have been reported in patients treated with levetiracetam. The median time of onset is reported to be 14 to 17 days, but cases have been reported at least four months after initiation of treatment. Recurrence of the serious skin reactions following rechallenge with levetiracetam has also been reported. KEPPRA XR should be discontinued at the first sign of a rash, unless the rash is clearly not drug-related. If signs or symptoms suggest SJS/TEN, use of this drug should not be resumed and alternative therapy should be considered.

5.6 Drug Reaction with Eosinophilia and Systemic Symptoms (DRESS)/Multiorgan Hypersensitivity

Drug Reaction with Eosinophilia and Systemic Symptoms (DRESS), also known as multiorgan hypersensitivity, has been reported in patients taking antiepileptic drugs, including levetiracetam. These events can be fatal or life-threatening, particularly if diagnosis and treatment do not occur as early as possible. DRESS typically, although not exclusively, presents with fever, rash, lymphadenopathy, and/or facial swelling, in association with other organ system involvement, such as hepatitis, nephritis, hematological abnormalities, myocarditis, or myositis, sometimes resembling an acute viral infection. Eosinophilia is often present. Because this disorder is variable in its expression, other organ systems not noted here may be involved. It is important to note that early manifestations of hypersensitivity, such as fever or lymphadenopathy, may be present even though rash is not evident. If such signs or symptoms are present, the patient should be evaluated immediately. KEPPRA XR should be discontinued if an alternative etiology for the signs or symptoms cannot be established [see Contraindications (4)] .

5.7 Coordination Difficulties

Coordination difficulties were not observed in the KEPPRA XR controlled trial, however, the number of patients exposed to KEPPRA XR was considerably smaller than the number of patients exposed to immediate-release KEPPRA tablets in controlled trials. However, adverse reactions observed in the immediate-release KEPPRA controlled trials may also occur in patients receiving KEPPRA XR.

Immediate-Release KEPPRA Tablets

A total of 3.4% of adult KEPPRA-treated patients experienced coordination difficulties, (reported as either ataxia, abnormal gait, or incoordination) compared to 1.6% of placebo-treated patients. A total of 0.4% of patients in controlled trials discontinued KEPPRA treatment due to ataxia, compared to 0% of placebo-treated patients. In 0.7% of KEPPRA-treated patients and in 0.2% of placebo-treated patients, the dose was reduced due to coordination difficulties, while one of the KEPPRA-treated patients was hospitalized due to worsening of pre-existing ataxia. These events occurred most frequently within the first 4 weeks of treatment.

Patients should be monitored for these signs and symptoms and advised not to drive or operate machinery until they have gained sufficient experience on KEPPRA to gauge whether it could adversely affect their ability to drive or operate machinery.

5.8 Withdrawal Seizures

As with most antiepileptic drugs, KEPPRA XR should generally be withdrawn gradually because of the risk of increased seizure frequency and status epilepticus. If withdrawal is needed because of a serious adverse reaction, rapid discontinuation can be considered.

5.9 Hematologic Abnormalities

KEPPRA XR can cause hematologic abnormalities. Hematologic abnormalities occurred in clinical trials and included decreases in white blood cell (WBC), neutrophil, and red blood cell (RBC) counts; decreases in hemoglobin and hematocrit; and increases in eosinophil counts. Cases of agranulocytosis, pancytopenia, and thrombocytopenia have also been reported in the postmarketing setting. A complete blood count is recommended in patients experiencing significant weakness, pyrexia, recurrent infections, or coagulation disorders.

In controlled trials of immediate-release KEPPRA tablets in patients experiencing partial-onset seizures, minor, but statistically significant, decreases compared to placebo in total mean RBC count (0.03 × 10^6/mm^3), mean hemoglobin (0.09 g/dL), and mean hematocrit (0.38%), were seen in immediate-release KEPPRA-treated patients.

A total of 3.2% of KEPPRA-treated and 1.8% of placebo-treated patients had at least one possibly significant (≤2.8 × 10^9/L) decreased WBC, and 2.4% of KEPPRA-treated and 1.4% of placebo-treated patients had at least one possibly significant (≤1.0 × 10^9/L) decreased neutrophil count. Of the KEPPRA-treated patients with a low neutrophil count, all but one rose towards or to baseline with continued treatment. No patient was discontinued secondary to low neutrophil counts.

In pediatric patients (4 to <16 years of age), statistically significant decreases in WBC and neutrophil counts were seen in patients treated with immediate-release KEPPRA, as compared to placebo. The mean decreases from baseline in the immediate-release KEPPRA group were -0.4 × 10^9/L and -0.3 × 10^9/L, respectively, whereas there were small increases in the placebo group. A significant increase in mean relative lymphocyte counts was observed in 1.7% of patients treated with immediate-release KEPPRA compared to a decrease of 4% in patients on placebo.

In the controlled pediatric trial, a possibly clinically significant abnormal low WBC value was observed in 3% of patients treated with immediate-release KEPPRA, compared to no patients on placebo. However, there was no apparent difference between treatment groups with respect to neutrophil count. No patient was discontinued secondary to low WBC or neutrophil counts.

In the controlled pediatric cognitive and neuropsychological safety study, two subjects (6.1%) in the placebo group and 5 subjects (8.6%) in the immediate-release KEPPRA-treated group had high eosinophil count values that were possibly clinically significant (≥10% or ≥0.7×10^9/L).

5.10 Seizure Control During Pregnancy

Physiological changes may gradually decrease plasma levels of levetiracetam throughout pregnancy. This decrease is more pronounced during the third trimester. It is recommended that patients be monitored carefully during pregnancy. Close monitoring should continue through the postpartum period especially if the dose was changed during pregnancy.

6 ADVERSE REACTIONS

The following adverse reactions are discussed in more details in other sections of labeling:

- Behavioral abnormalities and Psychotic Symptoms [see Warnings and Precautions (5.1)]
- Suicidal Behavior and Ideation [see Warnings and Precautions (5.2)]
- Somnolence and Fatigue [see Warnings and Precautions (5.3)]
- Anaphylaxis and Angioedema [see Warnings and Precautions (5.4)]
- Serious Dermatological Reactions [see Warnings and Precautions (5.5)]
- Drug Reaction with Eosinophilia and Systemic Symptoms (DRESS)/Multiorgan Hypersensitivity [see Warnings and Precautions (5.6)]
- Coordination Difficulties [see Warnings and Precautions (5.7)]
- Hematologic Abnormalities [see Warnings and Precautions (5.9)]

6.1 Clinical Trials Experience

Because clinical trials are conducted under widely varying conditions, adverse reaction rates observed in the clinical trials of a drug cannot be directly compared to rates in the clinical trials of another drug and may not reflect the rates observed in practice.

KEPPRA XR Tablets

In the controlled clinical study in patients with partial-onset seizures [see Clinical Studies (14.1)],the most common adverse reactions in patients receiving KEPPRA XR in combination with other AEDs, for events with rates greater than placebo, were irritability and somnolence.

Table 3 lists adverse reactions that occurred in at least 5% of epilepsy patients receiving KEPPRA XR in the placebo-controlled study and were numerically more common than in patients treated with placebo. In this study, either KEPPRA XR or placebo was added to concurrent AED therapy.

Table 3: Adverse Reactions in the Placebo-Controlled, Adjunctive Study in Patients Experiencing Partial-Onset Seizures
 | KEPPRA XR (N=77) % | Placebo (N=79) %
Influenza | 8 | 4
Somnolence | 8 | 3
Irritability | 7 | 0
Nasopharyngitis | 7 | 5
Dizziness | 5 | 3
Nausea | 5 | 3

Discontinuation or Dose Reduction in the KEPPRA XR Controlled Clinical Study

In the controlled clinical study, 5% of patients receiving KEPPRA XR and 3% receiving placebo discontinued as a result of an adverse reaction. The adverse reactions that resulted in discontinuation and that occurred more frequently in KEPPRA XR-treated patients than in placebo-treated patients were asthenia, epilepsy, mouth ulceration, rash, and respiratory failure. Each of these adverse reactions led to discontinuation in a KEPPRA XR-treated patient and no placebo-treated patients.

Immediate-Release KEPPRA Tablets

Table 4 lists the adverse reactions in the controlled studies of immediate-release KEPPRA tablets in adult patients experiencing partial-onset seizures [see Clinical Studies (14.2)]. Although the pattern of adverse reactions in the KEPPRA XR study seems somewhat different from that seen in partial-onset seizure controlled studies for immediate-release KEPPRA tablets, this is possibly due to the much smaller number of patients in this study compared to the immediate-release tablet studies. The adverse reactions for KEPPRA XR are expected to be similar to those seen with immediate-release KEPPRA tablets.

Adults

In controlled clinical studies of immediate-release KEPPRA tablets as adjunctive therapy to other AEDs in adults with partial-onset seizures, the most common adverse reactions, for events with rates greater than placebo, were somnolence, asthenia, infection, and dizziness.

Table 4 lists adverse reactions that occurred in at least 1% of adult epilepsy patients receiving immediate-release KEPPRA tablets in placebo-controlled studies and were numerically more common than in patients treated with placebo. In these studies, either immediate-release KEPPRA tablets or placebo was added to concurrent AED therapy.

Table 4: Adverse Reactions in Pooled Placebo-Controlled, Adjunctive Studies in Adults Experiencing Partial-Onset Seizures
 | KEPPRA (N=769) % | Placebo (N=439) %
Asthenia | 15 | 9
Somnolence | 15 | 8
Headache | 14 | 13
Infection | 13 | 8
Dizziness | 9 | 4
Pain | 7 | 6
Pharyngitis | 6 | 4
Depression | 4 | 2
Nervousness | 4 | 2
Rhinitis | 4 | 3
Anorexia | 3 | 2
Ataxia | 3 | 1
Vertigo | 3 | 1
Amnesia | 2 | 1
Anxiety | 2 | 1
Cough Increased | 2 | 1
Diplopia | 2 | 1
Emotional Lability | 2 | 0
Hostility | 2 | 1
Paresthesia | 2 | 1
Sinusitis | 2 | 1

Pediatric Patients 4 Years to <16 Years

In a pooled analysis of two controlled pediatric clinical studies in children 4 to 16 years of age with partial-onset seizures [see Clinical Studies (14.3)] , the adverse reactions most frequently reported with the use of immediate-release KEPPRA in combination with other AEDs, and with greater frequency than in patients on placebo, were fatigue, aggression, nasal congestion, decreased appetite, and irritability.

Table 5 lists adverse reactions that occurred in at least 2% of pediatric patients treated with immediate-release KEPPRA and were more common than in pediatric patients on placebo. In these studies, either immediate-release KEPPRA or placebo was added to concurrent AED therapy. Adverse reactions were usually mild to moderate in intensity.

Table 5: Adverse Reactions in Pooled Placebo-Controlled, Adjunctive Studies in Pediatric Patients Ages 4 to 16 Years Experiencing Partial-Onset Seizures
 | KEPPRA (N=165) % | Placebo (N=131) %
Headache | 19 | 15
Nasopharyngitis | 15 | 12
Vomiting | 15 | 12
Somnolence | 13 | 9
Fatigue | 11 | 5
Aggression | 10 | 5
Upper Abdominal Pain | 9 | 8
Cough | 9 | 5
Nasal Congestion | 9 | 2
Decreased Appetite | 8 | 2
Abnormal Behavior | 7 | 4
Dizziness | 7 | 5
Irritability | 7 | 1
Pharyngolaryngeal Pain | 7 | 4
Diarrhea | 6 | 2
Lethargy | 6 | 5
Insomnia | 5 | 3
Agitation | 4 | 1
Anorexia | 4 | 3
Head Injury | 4 | 0
Constipation | 3 | 1
Contusion | 3 | 1
Depression | 3 | 1
Fall | 3 | 2
Influenza | 3 | 1
Mood Altered | 3 | 1
Affect Lability | 2 | 1
Anxiety | 2 | 1
Arthralgia | 2 | 0
Confusional State | 2 | 0
Conjunctivitis | 2 | 0
Ear Pain | 2 | 1
Gastroenteritis | 2 | 0
Joint Sprain | 2 | 1
Mood Swings | 2 | 1
Neck Pain | 2 | 1
Rhinitis | 2 | 0
Sedation | 2 | 1

In controlled pediatric clinical studies in patients 4-16 years of age, 7% of patients treated with immediate-release KEPPRA tablets and 9% of patients on placebo discontinued as a result of an adverse event.

In addition, the following adverse reactions were seen in other controlled studies of immediate-release KEPPRA tablets: balance disorder, disturbance in attention, eczema, hyperkinesia, memory impairment, myalgia, personality disorders, pruritus, and blurred vision.

Comparison of Gender, Age and Race

There are insufficient data for KEPPRA XR to support a statement regarding the distribution of adverse reactions by gender, age, and race.

6.2 Postmarketing Experience

The following adverse reactions have been identified during postapproval use of immediate-release KEPPRA tablets. Because these reactions are reported voluntarily from a population of uncertain size, it is not always possible to reliably estimate their frequency or establish a causal relationship to drug exposure.

The listing is alphabetized: abnormal liver function test, acute kidney injury, anaphylaxis, angioedema, agranulocytosis, choreoathetosis, drug reaction with eosinophilia and systemic symptoms (DRESS), dyskinesia, erythema multiforme, hepatic failure, hepatitis, hyponatremia, muscular weakness, obsessive-compulsive disorders (OCD), pancreatitis, pancytopenia (with bone marrow suppression identified in some of these cases), panic attack, thrombocytopenia, weight loss, and worsening of seizures including in patients with SCN8A mutations. Alopecia has been reported with immediate-release KEPPRA use; recovery was observed in majority of cases where immediate-release KEPPRA was discontinued.

8 USE IN SPECIFIC POPULATIONS

8.1 Pregnancy

Pregnancy Exposure Registry

There is a pregnancy exposure registry that monitors pregnancy outcomes in women exposed to antiepileptic drugs (AEDs), including KEPPRA XR, during pregnancy. Encourage women who are taking KEPPRA XR during pregnancy to enroll in the North American Antiepileptic Drug (NAAED) pregnancy registry by calling 1-888-233-2334 or visiting http://www.aedpregnancyregistry.org/.

Risk Summary

Prolonged experience with KEPPRA in pregnant women has not identified a drug-associated risk of major birth defects or miscarriage, based on published literature, which includes data from pregnancy registries and reflects experience over two decades [see Human Data] . In animal studies, levetiracetam produced developmental toxicity (increased embryofetal and offspring mortality, increased incidences of fetal structural abnormalities, decreased embryofetal and offspring growth, neurobehavioral alterations in offspring) at doses similar to human therapeutic doses [see Animal Data].

In the U.S. general population, the estimated background risk of major birth defects and miscarriage in clinically recognized pregnancies is 2-4% and 15-20%, respectively. The background risk of major birth defects and miscarriage for the indicated population is unknown.

Clinical Considerations

KEPPRA XR levels may decrease during pregnancy [see Warnings and Precautions (5.10)].

Physiological changes during pregnancy may affect levetiracetam concentration. Decrease in levetiracetam plasma concentrations has been observed during pregnancy. This decrease is more pronounced during the third trimester. Dose adjustments may be necessary to maintain clinical response.

Data

Human Data

While available studies cannot definitively establish the absence of risk, data from the published literature and pregnancy registries have not established an association with levetiracetam use during pregnancy and major birth defects or miscarriage.

Animal Data

When levetiracetam (0, 400, 1200, or 3600 mg/kg/day) was administered orally to pregnant rats during the period of organogenesis, reduced fetal weights and increased incidence of fetal skeletal variations were observed at the highest dose tested. There was no evidence of maternal toxicity. The no-effect dose for adverse effects on embryofetal developmental in rats (1200 mg/kg/day) is approximately 4 times the maximum recommended human dose (MRHD) of 3000 mg on a body surface area (mg/m^2) basis.

Oral administration of levetiracetam (0, 200, 600, or 1800 mg/kg/day) to pregnant rabbits during the period of organogenesis resulted in increased embryofetal mortality and incidence of fetal skeletal variations at the mid and high dose and decreased fetal weights and increased incidence of fetal malformations at the high dose, which was associated with maternal toxicity. The no-effect dose for adverse effects on embryofetal development in rabbits (200 mg/kg/day) is approximately equivalent to the MRHD on a mg/m^2basis.

Oral administration of levetiracetam (0, 70, 350, or 1800 mg/kg/day) to female rats throughout pregnancy and lactation led to an increased incidence of fetal skeletal variations, reduced fetal body weight, and decreased growth in offspring at the mid and high doses and increased pup mortality and neurobehavioral alterations in offspring at the highest dose tested. There was no evidence of maternal toxicity. The no-effect dose for adverse effects on pre- and postnatal development in rats (70 mg/kg/day) is less than the MRHD on a mg/m^2basis.

Oral administration of levetiracetam to rats during the latter part of gestation and throughout lactation produced no adverse developmental or maternal effects at doses of up to 1800 mg/kg/day (6 times the MRHD on a mg/m^2basis).

8.2 Lactation

Risk Summary

Levetiracetam is excreted in human milk. There are no data on the effects of KEPPRA XR on the breastfed infant, or the effects on milk production.

The developmental and health benefits of breastfeeding should be considered along with the mother's clinical need for KEPPRA XR and any potential adverse effects on the breastfed infant from KEPPRA XR or from the underlying maternal condition.

8.4 Pediatric Use

Safety and effectiveness in patients 12 years of age and older have been established based on pharmacokinetic data in adults and adolescents using KEPPRA XR and efficacy and safety data in controlled pediatric studies using immediate-release KEPPRA [see Adverse Reactions (6.1), Clinical Pharmacology (12.3), and Clinical Studies (14.1)].

Safety and effectiveness in pediatric patients below the age of 12 have not been established.

A 3-month, randomized, double-blind, placebo-controlled study was performed to assess the neurocognitive and behavioral effects of immediate-release KEPPRA as adjunctive therapy in 98 pediatric patients with inadequately controlled partial seizures, ages 4 to 16 years (KEPPRA N=64; placebo N=34). The target dose of immediate-release KEPPRA was 60 mg/kg/day. Neurocognitive effects were measured by the Leiter-R Attention and Memory (AM) Battery, which assesses various aspects of a child's memory and attention. Although no substantive differences were observed between the placebo- and KEPPRA-treated groups in the median change from baseline in this battery, the study was not adequate to assess formal statistical non-inferiority between the drug and placebo. The Achenbach Child Behavior Checklist (CBCL/6-18), a standardized validated tool used to assess a child's competencies and behavioral/emotional problems, was also assessed in this study. An analysis of the CBCL/6-18 indicated a worsening in aggressive behavior, one of the eight syndrome scores, in patients treated with KEPPRA [see Warnings and Precautions (5.1)] .

Juvenile Animal Toxicity Data

Studies of levetiracetam in juvenile rats (dosed on postnatal days 4 through 52) and dogs (dosed from postnatal weeks 3 through 7) at doses of up to 1800 mg/kg/day (approximately 7 and 24 times, respectively, the maximum recommended pediatric dose of 60 mg/kg/day on a mg/m^2basis) did not demonstrate adverse effects on postnatal development.

8.5 Geriatric Use

There were insufficient numbers of elderly subjects in controlled trials of epilepsy to adequately assess the effectiveness of KEPPRA XR in these patients. It is expected that the safety of KEPPRA XR in elderly patients 65 and over would be comparable to the safety observed in clinical studies of immediate-release KEPPRA tablets.

There were 347 subjects in clinical studies of immediate-release KEPPRA that were 65 and over. No overall differences in safety were observed between these subjects and younger subjects. There were insufficient numbers of elderly subjects in controlled trials of epilepsy to adequately assess the effectiveness of immediate-release KEPPRA in these patients.

Levetiracetam is known to be substantially excreted by the kidney, and the risk of adverse reactions to this drug may be greater in patients with impaired renal function. Because elderly patients are more likely to have decreased renal function, care should be taken in dose selection, and it may be useful to monitor renal function [see Clinical Pharmacology (12.3)] .

8.6 Renal Impairment

The effect of KEPPRA XR on renally impaired patients was not assessed in the controlled study. However, it is expected that the effect on KEPPRA XR-treated patients would be similar to the effect seen in controlled studies of immediate-release KEPPRA tablets. Clearance of levetiracetam is decreased in patients with renal impairment and is correlated with creatinine clearance [see Clinical Pharmacology (12.3)] . Dose adjustment is recommended for patients with impaired renal function [see Dosage and Administration (2.2)] .

10 OVERDOSAGE

10.1 Signs, Symptoms and Laboratory Findings of Acute Overdosage in Humans

The signs and symptoms for KEPPRA XR overdose are expected to be similar to those seen with immediate-release KEPPRA tablets.

The highest known dose of oral immediate-release KEPPRA received in the clinical development program was 6000 mg/day. Other than drowsiness, there were no adverse reactions in the few known cases of overdose in clinical trials. Cases of somnolence, agitation, aggression, depressed level of consciousness, respiratory depression and coma were observed with immediate-release KEPPRA overdoses in postmarketing use.

10.2 Management of Overdose

There is no specific antidote for overdose with KEPPRA XR. If indicated, elimination of unabsorbed drug should be attempted by emesis or gastric lavage; usual precautions should be observed to maintain airway. General supportive care of the patient is indicated including monitoring of vital signs and observation of the patient's clinical status. A Certified Poison Control Center should be contacted for up to date information on the management of overdose with KEPPRA XR.

10.3 Hemodialysis

Standard hemodialysis procedures result in significant clearance of levetiracetam (approximately 50% in 4 hours) and should be considered in cases of overdose. Although hemodialysis has not been performed in the few known cases of overdose, it may be indicated by the patient's clinical state or in patients with significant renal impairment.

11 DESCRIPTION

KEPPRA XR is an antiepileptic drug available as 500 mg and 750 mg (white) extended-release tablets for oral administration.

The chemical name of levetiracetam, a single enantiomer, is (-)-(S)-α-ethyl-2-oxo-1-pyrrolidine acetamide, its molecular formula is C8H14N2O2and its molecular weight is 170.21. Levetiracetam is chemically unrelated to existing antiepileptic drugs (AEDs). It has the following structural formula:

Levetiracetam is a white to off-white crystalline powder with a faint odor and a bitter taste. It is very soluble in water (104.0 g/100 mL). It is freely soluble in chloroform (65.3 g/100 mL) and in methanol (53.6 g/100 mL), soluble in ethanol (16.5 g/100 mL), sparingly soluble in acetonitrile (5.7 g/100 mL) and practically insoluble in n-hexane. (Solubility limits are expressed as g/100 mL solvent.)

KEPPRA XR tablets contain the labeled amount of levetiracetam. Inactive ingredients: colloidal anhydrous silica, hypromellose, magnesium stearate, polyethylene glycol 6000, polyvinyl alcohol-partially hydrolyzed, titanium dioxide (E171), Macrogol/PEG3350, and talc. The imprinting ink contains shellac, FD&C Red #40, n-butyl alcohol, propylene glycol, titanium dioxide, ethanol, and methanol.

The medication is combined with a drug release controlling polymer that provides a drug release at a controlled rate. The biologically inert components of the tablet may occasionally remain intact during GI transit and will be eliminated in the feces as a soft, hydrated mass.

12 CLINICAL PHARMACOLOGY

12.1 Mechanism of Action

The precise mechanism(s) by which levetiracetam exerts its antiepileptic effect is unknown.

A saturable and stereoselective neuronal binding site in rat brain tissue has been described for levetiracetam. Experimental data indicate that this binding site is the synaptic vesicle protein SV2A, thought to be involved in the regulation of vesicle exocytosis. Although the molecular significance of levetiracetam binding to synaptic vesicle protein SV2A is not understood, levetiracetam and related analogs showed a rank order of affinity for SV2A which correlated with the potency of their antiseizure activity in audiogenic seizure-prone mice. These findings suggest that the interaction of levetiracetam with the SV2A protein may contribute to the antiepileptic mechanism of action of the drug.

12.2 Pharmacodynamics

Effects on QTc Interval

The effects of KEPPRA XR on QTc prolongation is expected to be the same as that of immediate-release KEPPRA. The effect of immediate-release KEPPRA on QTc prolongation was evaluated in a randomized, double-blind, positive-controlled (moxifloxacin 400 mg) and placebo-controlled crossover study of KEPPRA (1000 mg or 5000 mg) in 52 healthy subjects. The upper bound of the 90% confidence interval for the largest placebo-adjusted, baseline-corrected QTc was below 10 milliseconds. Therefore, there was no evidence of significant QTc prolongation in this study.

12.3 Pharmacokinetics

Overview

Bioavailability of KEPPRA XR tablets is similar to that of the immediate-release KEPPRA tablets. The pharmacokinetics (AUC and Cmax) were shown to be dose proportional after single dose administration of 1000 mg, 2000 mg, and 3000 mg extended-release levetiracetam. Plasma half-life of extended-release levetiracetam is approximately 7 hours.

Levetiracetam is almost completely absorbed after oral administration. The pharmacokinetics of levetiracetam are linear and time-invariant, with low intra- and inter-subject variability. Levetiracetam is not significantly protein-bound (<10% bound) and its volume of distribution is close to the volume of intracellular and extracellular water. Sixty-six percent (66%) of the dose is renally excreted unchanged. The major metabolic pathway of levetiracetam (24% of dose) is an enzymatic hydrolysis of the acetamide group. It is not liver cytochrome P450 dependent. The metabolites have no known pharmacological activity and are renally excreted. Plasma half-life of levetiracetam across studies is approximately 6-8 hours. The half-life is increased in the elderly (primarily due to impaired renal clearance) and in subjects with renal impairment.

The pharmacokinetics of levetiracetam are similar when used as monotherapy or as adjunctive therapy for the treatment of partial-onset seizures.

Absorption and Distribution

Extended-release levetiracetam peak plasma concentrations occur in about 4 hours. The time to peak plasma concentrations is about 3 hours longer with extended-release levetiracetam than with immediate-release tablets.

Single administration of two 500 mg extended-release levetiracetam tablets once daily produced comparable maximal plasma concentrations and area under the plasma concentration versus time as did the administration of one 500 mg immediate-release tablet twice daily in fasting conditions. After multiple dose extended-release levetiracetam tablets intake, extent of exposure (AUC0-24) was similar to extent of exposure after multiple dose immediate-release tablets intake. Cmaxand Cminwere lower by 17% and 26% after multiple dose extended-release levetiracetam tablets intake in comparison to multiple dose immediate-release tablets intake. Intake of a high fat, high calorie breakfast before the administration of extended-release levetiracetam tablets resulted in a higher peak concentration, and longer median time to peak. The median time to peak (Tmax) was 2 hours longer in the fed state.

Two 750 mg extended-release levetiracetam tablets were bioequivalent to a single administration of three 500 mg extended-release levetiracetam tablets.

Metabolism

Levetiracetam is not extensively metabolized in humans. The major metabolic pathway is the enzymatic hydrolysis of the acetamide group, which produces the carboxylic acid metabolite, ucb L057 (24% of dose) and is not dependent on any liver cytochrome P450 isoenzymes. The major metabolite is inactive in animal seizure models. Two minor metabolites were identified as the product of hydroxylation of the 2-oxo-pyrrolidine ring (2% of dose) and opening of the 2-oxo-pyrrolidine ring in position 5 (1% of dose). There is no enantiomeric interconversion of levetiracetam or its major metabolite.

Elimination

Levetiracetam plasma half-life in adults is 7 ± 1 hour and is unaffected by either dose or repeated administration. Levetiracetam is eliminated from the systemic circulation by renal excretion as unchanged drug which represents 66% of administered dose. The total body clearance is 0.96 mL/min/kg and the renal clearance is 0.6 mL/min/kg. The mechanism of excretion is glomerular filtration with subsequent partial tubular reabsorption. The metabolite ucb L057 is excreted by glomerular filtration and active tubular secretion with a renal clearance of 4 mL/min/kg. Levetiracetam elimination is correlated to creatinine clearance. Levetiracetam clearance is reduced in patients with impaired renal function [see Dosage and Administration (2.2)and Use in Specific Populations (8.6)] .

Specific Populations

Elderly

There are insufficient pharmacokinetic data to specifically address the use of extended-release levetiracetam in the elderly population.

Pharmacokinetics of immediate-release levetiracetam were evaluated in 16 elderly subjects (age 61-88 years) with creatinine clearance ranging from 30 to 74 mL/min. Following oral administration of twice-daily dosing for 10 days, total body clearance decreased by 38% and the half-life was 2.5 hours longer in the elderly compared to healthy adults. This is most likely due to the decrease in renal function in these subjects.

Pediatric Patients

An open label, multicenter, parallel-group, two-arm study was conducted to evaluate the pharmacokinetics of KEPPRA XR in pediatric patients (13 to 16 years old) and in adults (18 to 55 years old) with epilepsy. KEPPRA XR oral tablets (1000 mg to 3000 mg) were administered once daily with a minimum of 4 days and a maximum of 7 days of treatment to 12 pediatric patients and 13 adults in the study. Dose-normalized steady-state exposure parameters, Cmaxand AUC, were comparable between pediatric and adult patients.

Pregnancy

KEPPRA XR levels may decrease during pregnancy [see Warnings and Precautions (5.10)and Use in Specific Populations (8.1)] .

Gender

Extended-release levetiracetam Cmaxwas 21-30% higher and AUC was 8-18% higher in women (N=12) compared to men (N=12). However, clearances adjusted for body weight were comparable.

Race

Formal pharmacokinetic studies of the effects of race have not been conducted with extended-release or immediate-release levetiracetam. Cross study comparisons involving Caucasians (N=12) and Asians (N=12), however, show that pharmacokinetics of immediate-release levetiracetam were comparable between the two races. Because levetiracetam is primarily renally excreted and there are no important racial differences in creatinine clearance, pharmacokinetic differences due to race are not expected.

Renal Impairment

The effect of KEPPRA XR on renally impaired patients was not assessed in the controlled study. However, it is expected that the effect on KEPPRA XR-treated patients would be similar to that seen in controlled studies of immediate-release KEPPRA tablets. In patients with end stage renal disease on dialysis, it is recommended that immediate-release KEPPRA be used instead of KEPPRA XR.

The disposition of immediate-release levetiracetam was studied in adult subjects with varying degrees of renal function. Total body clearance of levetiracetam is reduced in patients with impaired renal function by 40% in the mild group (CLcr = 50-80 mL/min), 50% in the moderate group (CLcr = 30-50 mL/min) and 60% in the severe renal impairment group (CLcr <30 mL/min). Clearance of levetiracetam is correlated with creatinine clearance.

In anuric (end stage renal disease) patients, the total body clearance decreased 70% compared to normal subjects (CLcr >80mL/min). Approximately 50% of the pool of levetiracetam in the body is removed during a standard 4- hour hemodialysis procedure [see Dosage and Administration (2.2)] .

Hepatic Impairment

In subjects with mild (Child-Pugh A) to moderate (Child-Pugh B) hepatic impairment, the pharmacokinetics of levetiracetam were unchanged. In patients with severe hepatic impairment (Child-Pugh C), total body clearance was 50% that of normal subjects, but decreased renal clearance accounted for most of the decrease. No dose adjustment is needed for patients with hepatic impairment.

Drug Interactions

In vitrodata on metabolic interactions indicate that levetiracetam is unlikely to produce, or be subject to, pharmacokinetic interactions. Levetiracetam and its major metabolite, at concentrations well above Cmaxlevels achieved within the therapeutic dose range, are neither inhibitors of, nor high affinity substrates for, human liver cytochrome P450 isoforms, epoxide hydrolase or UDP-glucuronidation enzymes. In addition, levetiracetam does not affect the in vitroglucuronidation of valproic acid.

Potential pharmacokinetic interactions of or with levetiracetam were assessed in clinical pharmacokinetic studies (phenytoin, valproate, warfarin, digoxin, oral contraceptive, probenecid) and through pharmacokinetic screening with immediate-release KEPPRA tablets in the placebo-controlled clinical studies in epilepsy patients. The potential for drug interactions for KEPPRA XR is expected to be essentially the same as that with immediate-release KEPPRA tablets.

Phenytoin

Immediate-release KEPPRA tablets (3000 mg daily) had no effect on the pharmacokinetic disposition of phenytoin in patients with refractory epilepsy. Pharmacokinetics of levetiracetam were also not affected by phenytoin.

Valproate

Immediate-release KEPPRA tablets (1500 mg twice daily) did not alter the pharmacokinetics of valproate in healthy volunteers. Valproate 500 mg twice daily did not modify the rate or extent of levetiracetam absorption or its plasma clearance or urinary excretion. There also was no effect on exposure to and the excretion of the primary metabolite, ucb L057.

Other Antiepileptic Drugs

Potential drug interactions between immediate-release KEPPRA tablets and other AEDs (carbamazepine, gabapentin, lamotrigine, phenobarbital, phenytoin, primidone and valproate) were also assessed by evaluating the serum concentrations of levetiracetam and these AEDs during placebo-controlled clinical studies. These data indicate that levetiracetam does not influence the plasma concentration of other AEDs and that these AEDs do not influence the pharmacokinetics of levetiracetam.

Oral Contraceptives

Immediate-release KEPPRA tablets (500 mg twice daily) did not influence the pharmacokinetics of an oral contraceptive containing 0.03 mg ethinyl estradiol and 0.15 mg levonorgestrel, or of the luteinizing hormone and progesterone levels, indicating that impairment of contraceptive efficacy is unlikely. Coadministration of this oral contraceptive did not influence the pharmacokinetics of levetiracetam.

Digoxin

Immediate-release KEPPRA tablets (1000 mg twice daily) did not influence the pharmacokinetics and pharmacodynamics (ECG) of digoxin given as a 0.25 mg dose every day. Coadministration of digoxin did not influence the pharmacokinetics of levetiracetam.

Warfarin

Immediate-release KEPPRA tablets (1000 mg twice daily) did not influence the pharmacokinetics of R and S warfarin. Prothrombin time was not affected by levetiracetam. Coadministration of warfarin did not affect the pharmacokinetics of levetiracetam.

Probenecid

Probenecid, a renal tubular secretion blocking agent, administered at a dose of 500 mg four times a day, did not change the pharmacokinetics of levetiracetam 1000 mg twice daily. Cssmaxof the metabolite, ucb L057, was approximately doubled in the presence of probenecid while the fraction of drug excreted unchanged in the urine remained the same. Renal clearance of ucb L057 in the presence of probenecid decreased 60%, probably related to competitive inhibition of tubular secretion of ucb L057. The effect of immediate-release KEPPRA tablets on probenecid was not studied.

13 NONCLINICAL TOXICOLOGY

13.1 Carcinogenesis, Mutagenesis, Impairment of Fertility

Carcinogenesis

Rats were dosed with levetiracetam in the diet for 104 weeks at doses of 50, 300, and 1800 mg/kg/day. Plasma exposure (AUC) at the highest dose was approximately 6 times that in humans at the maximum recommended daily human dose (MRHD) of 3000 mg. There was no evidence of carcinogenicity. In mice, oral administration of levetiracetam for 80 weeks (doses up to 960 mg/kg/day) or 2 years (doses up to 4000 mg/kg/day, lowered to 3000 mg/kg/day after 45 weeks due to intolerability) was not associated with an increase in tumors. The highest dose tested in mice for 2 years (3000 mg/kg/day) is approximately 5 times the MRHD on a body surface area (mg/m^2) basis.

Mutagenesis

Levetiracetam was negative in in vitro(Ames, chromosomal aberration in mammalian cells) and in vivo(mouse micronucleus) assays. The major human metabolite of levetiracetam (ucb L057) was negative in in vitro(Ames, mouse lymphoma) assays.

Impairment of Fertility

No adverse effects on male or female fertility or reproductive performance were observed in rats at oral doses up to 1800 mg/kg/day, which were associated with plasma exposures (AUC) up to approximately 6 times that in humans at the MRHD.

14 CLINICAL STUDIES

The effectiveness of KEPPRA XR for the treatment of partial-onset seizures in adults was established in one multicenter, randomized, double-blind, placebo-controlled clinical study in patients who had refractory partial-onset seizures with or without secondary generalization. This was supported by the demonstration of efficacy of immediate-release KEPPRA tablets (see below) in partial seizures in three multicenter, randomized, double-blind, placebo-controlled clinical studies in adults, as well as a demonstration of comparable bioavailability between the XR and immediate-release formulations [see Clinical Pharmacology (12.3)] in adults. The effectiveness for KEPPRA XR for the treatment of partial-onset seizures in pediatric patients, 12 years of age and older, was based upon a single pharmacokinetic study showing comparable pharmacokinetics of KEPPRA XR in adults and adolescents [see Clinical Pharmacology (12.3)] . All studies are described below.

14.1 KEPPRA XR in Adults

The effectiveness of KEPPRA XR for the treatment of partial-onset seizures in adults was established in one multicenter, randomized, double-blind, placebo-controlled clinical study across 7 countries in patients who had refractory partial-onset seizures with or without secondary generalization (Study 1).

Study 1

Patients enrolled in Study 1 had at least eight partial seizures with or without secondary generalization during the 8-week baseline period and at least two partial seizures in each 4-week interval of the baseline period. Patients were taking a stable dose regimen of at least one AED and could take a maximum of three AEDs. After a prospective baseline period of 8 weeks, 158 patients were randomized to placebo (N=79) or 1000 mg (two 500 mg tablets) of KEPPRA XR (N=79), given once daily over a 12-week treatment period.

The primary efficacy endpoint in Study 1 was the percent reduction over placebo in mean weekly frequency of partial-onset seizures. The median percent reduction in weekly partial-onset seizure frequency from baseline over the treatment period was 46.1% in the KEPPRA XR 1000 mg treatment group (N=74) and 33.4% in the placebo group (N=78). The estimated percent reduction over placebo in weekly partial-onset seizure frequency over the treatment period was 14.4% (statistically significant).

The relationship between the effectiveness of the same daily dose of KEPPRA XR and immediate-release KEPPRA has not been studied and is unknown.

14.2 Immediate-Release KEPPRA in Adults

The effectiveness of immediate-release KEPPRA for the treatment of partial-onset seizures in adults was established in three multicenter, randomized, double-blind, placebo-controlled clinical studies in patients who had refractory partial-onset seizures with or without secondary generalization (Studies 2, 3, and 4). The tablet formulation was used in all three studies. In these studies, 904 patients were randomized to placebo, KEPPRA 1000 mg, KEPPRA 2000 mg, or KEPPRA 3000 mg/day. Patients enrolled in Study 2 or Study 3 had refractory partial-onset seizures for at least two years and had taken two or more AEDs. Patients enrolled in Study 4 had refractory partial-onset seizures for at least 1 year and had taken one AED. At the time of the study, patients were taking a stable dose regimen of at least one AED and could take a maximum of two AEDs. During the baseline period, patients had to have experienced at least two partial-onset seizures during each 4-week period.

Study 2

Study 2 was a double-blind, placebo-controlled, parallel-group study conducted at 41 sites in the United States, comparing immediate-release KEPPRA 1000 mg/day (N=97), immediate-release KEPPRA 3000 mg/day (N=101), and placebo (N=95), given in equally divided doses twice daily. After a prospective baseline period of 12 weeks, patients in Study 2 were randomized to one of the three treatment groups described above. The 18-week treatment period consisted of a 6-week titration period, followed by a 12-week fixed dose evaluation period, during which concomitant AED regimens were held constant. The primary measure of effectiveness in Study 2 was a between-group comparison of the percent reduction in weekly partial seizure frequency relative to placebo over the entire randomized treatment period (titration + evaluation period). Secondary outcome variables included the responder rate (incidence of patients with ≥50% reduction from baseline in partial-onset seizure frequency). The results of Study 2 are displayed in Table 6.

Table 6: Reduction In Mean Over Placebo In Weekly Frequency Of Partial-Onset Seizures In Study 2
 | Placebo (N=95) | Immediate-release KEPPRA 1000 mg/day (N=97) | Immediate-release KEPPRA 3000 mg/day (N=101)
Percent reduction in partial seizure frequency over placebo | – | 26.1% [statistically significant versus placebo] | 30.1%

The percentage of patients (y-axis) who achieved ≥50% reduction from baseline in weekly partial-onset seizure frequency over the entire randomized treatment period (titration + evaluation period) within the three treatment groups (x-axis) in Study 2 is presented in Figure 1.

Figure 1: Responder Rate (≥50% Reduction From Baseline) In Study 2

* statistically significant versus placebo

Study 3

Study 3 was a double-blind, placebo-controlled, crossover study conducted at 62 centers in Europe, comparing immediate-release KEPPRA 1000 mg/day (N=106), immediate-release KEPPRA 2000 mg/day (N=105), and placebo (N=111), given in equally divided doses twice daily.

The first period of the study (Period A) was designed to be analyzed as a parallel-group study. After a prospective baseline period of up to 12 weeks, patients in Study 3 were randomized to one of the three treatment groups described above. The 16-week treatment period consisted of the 4-week titration period followed by a 12-week fixed dose evaluation period, during which concomitant AED regimens were held constant. The primary measure of effectiveness in Study 3 was a between group comparison of the percent reduction in weekly partial seizure frequency relative to placebo over the entire randomized treatment period (titration + evaluation period). Secondary outcome variables included the responder rate (incidence of patients with ≥50% reduction from baseline in partial-onset seizure frequency). The results of the analysis of Period A are displayed in Table 7.

Table 7: Reduction In Mean Over Placebo In Weekly Frequency Of Partial-Onset Seizures In Study 3: Period A
 | Placebo (N=111) | Immediate-release KEPPRA 1000 mg/day (N=106) | Immediate-release KEPPRA 2000 mg/day (N=105)
Percent reduction in partial seizure frequency over placebo | – | 17.1% [statistically significant versus placebo] | 21.4%

The percentage of patients (y-axis) who achieved ≥50% reduction from baseline in weekly partial-onset seizure frequency over the entire randomized treatment period (titration + evaluation period) within the three treatment groups (x-axis) in Study 3 is presented in Figure 2.

Figure 2: Responder Rate (≥50% Reduction From Baseline) In Study 3: Period A

* statistically significant versus placebo

The comparison of immediate-release KEPPRA 2000 mg/day to immediate-release KEPPRA 1000 mg/day for responder rate in Study 3 was statistically significant (P=0.02). Analysis of the trial as a cross-over study yielded similar results.

Study 4

Study 4 was a double-blind, placebo-controlled, parallel-group study conducted at 47 centers in Europe comparing immediate-release KEPPRA 3000 mg/day (N=180) and placebo (N=104) in patients with refractory partial-onset seizures, with or without secondary generalization, receiving only one concomitant AED. Study drug was given in two divided doses. After a prospective baseline period of 12 weeks, patients in Study 4 were randomized to one of two treatment groups described above. The 16-week treatment period consisted of a 4-week titration period, followed by a 12-week fixed dose evaluation period, during which concomitant AED doses were held constant. The primary measure of effectiveness in Study 4 was a between group comparison of the percent reduction in weekly seizure frequency relative to placebo over the entire randomized treatment period (titration + evaluation period). Secondary outcome variables included the responder rate (incidence of patients with ≥50% reduction from baseline in partial-onset seizure frequency). Table 8 displays the results of Study 4.

Table 8: Reduction In Mean Over Placebo In Weekly Frequency Of Partial-Onset Seizures In Study 4
 | Placebo (N=104) | Immediate-release KEPPRA 3000 mg/day (N=180)
Percent reduction in partial seizure frequency over placebo | – | 23.0% [statistically significant versus placebo]

The percentage of patients (y-axis) who achieved ≥50% reduction from baseline in weekly partial-onset seizure frequency over the entire randomized treatment period (titration + evaluation period) within the two treatment groups (x-axis) in Study 4 is presented in Figure 3.

Figure 3: Responder Rate (≥50% Reduction From Baseline) In Study 4

* statistically significant versus placebo

14.3 Immediate-Release KEPPRA in Pediatric Patients 4 Years to 16 Years

The use of KEPPRA XR in pediatric patients 12 years of age and older is supported by Study 5, which was conducted using immediate-release KEPPRA. KEPPRA XR is not indicated in children below 12 years of age.

Study 5

The effectiveness of immediate-release KEPPRA for the treatment of partial-onset seizures in pediatric patients was established in a multicenter, randomized double-blind, placebo-controlled study, conducted at 60 sites in North America, in children 4 to 16 years of age with partial seizures uncontrolled by standard antiepileptic drugs (Study 5). Eligible patients on a stable dose of 1-2 AEDs, who still experienced at least 4 partial-onset seizures during the 4 weeks prior to screening, as well as at least 4 partial-onset seizures in each of the two 4-week baseline periods, were randomized to receive either immediate-release KEPPRA or placebo. The enrolled population included 198 patients (KEPPRA N=101; placebo N=97) with refractory partial-onset seizures, with or without secondarily generalization. Study 5 consisted of an 8-week baseline period and 4-week titration period followed by a 10-week evaluation period. Dosing was initiated at a dose of 20 mg/kg/day in two divided doses. During the treatment period, the immediate-release KEPPRA doses were adjusted in 20 mg/kg/day increments, at 2-week intervals to the target dose of 60 mg/kg/day. The primary measure of effectiveness in Study 5 was a between group comparison of the percent reduction in weekly partial seizure frequency relative to placebo over the entire 14-week randomized treatment period (titration + evaluation period). Secondary outcome variables included the responder rate (incidence of patients with ≥ 50% reduction from baseline in partial-onset seizure frequency per week). Table 9 displays the results of this study.

Table 9: Reduction In Mean Over Placebo In Weekly Frequency Of Partial-Onset Seizures in Study 5
 | Placebo (N=97) | Immediate-release KEPPRA (N=101)
Percent reduction in partial seizure frequency over placebo | - | 26.8% [statistically significant versus placebo]

The percentage of patients (y-axis) who achieved ≥ 50% reduction in weekly partial-onset seizure frequency over the entire randomized treatment period (titration + evaluation period) within the two treatment groups (x-axis) in Study 5 is presented in Figure 4.

Figure 4: Responder Rate (≥ 50% Reduction From Baseline) in Study 5

* statistically significant versus placebo

16 HOW SUPPLIED/STORAGE AND HANDLING

16.1 How Supplied

KEPPRA XR 500 mg tablets are white, oblong-shaped, film-coated tablets imprinted with "UCB 500XR" in red on one side. They are supplied in white HDPE bottles containing 60 tablets (NDC 50474-598-66).

KEPPRA XR 750 mg tablets are white, oblong-shaped, film-coated tablets imprinted with "UCB 750XR" in red on one side. They are supplied in white HDPE bottles containing 60 tablets (NDC 50474-599-66).

16.2 Storage

Store at 25°C (77°F); excursions permitted to 15°C to 30°C (59°F to 86°F) [see USP Controlled Room Temperature].

17 PATIENT COUNSELING INFORMATION

Advise the patient to read the FDA-approved patient labeling (Medication Guide). The Medication Guide accompanies the product and can also be accessed on www.keppraxr.com or by calling 1-844-599-2273.

Psychiatric Reactions and Changes in Behavior

Advise patients that KEPPRA XR may cause changes in behavior (e.g. irritability and aggression). In addition, patients should be advised that they may experience changes in behavior that have been seen with other formulations of KEPPRA, which include agitation, anger, anxiety, apathy, depression, hostility, and psychotic symptoms [see Warnings and Precautions (5.1)] .

Suicidal Behavior and Ideation

Counsel patients, their caregivers, and/or families that antiepileptic drugs (AEDs), including KEPPRA XR, may increase the risk of suicidal thoughts and behavior and advise patients to be alert for the emergence or worsening of symptoms of depression; unusual changes in mood or behavior; or suicidal thoughts, behavior, or thoughts about self-harm. Advise patients, their caregivers, and/or families to immediately report behaviors of concern to a healthcare provider [see Warnings and Precautions (5.2)] .

Effects on Driving or Operating Machinery

Inform patients that KEPPRA XR may cause dizziness and somnolence. Inform patients not to drive or operate machinery until they have gained sufficient experience on KEPPRA XR to gauge whether it adversely affects their ability to drive or operate machinery [see Warnings and Precautions (5.3)] .

Anaphylaxis and Angioedema

Advise patients to discontinue KEPPRA XR and seek medical care if they develop signs and symptoms of anaphylaxis or angioedema [see Warnings and Precautions (5.4)].

Dermatological Adverse Reactions

Advise patients that serious dermatological adverse reactions have occurred in patients treated with levetiracetam and instruct them to call their physician immediately if a rash develops [see Warnings and Precautions (5.5)] .

DRESS/Multiorgan Hypersensitivity

Instruct patients and caregivers that a fever or rash associated with signs of other organ system involvement (e.g., lymphadenopathy, hepatic dysfunction) may be drug-related and should be reported to their healthcare provider immediately. KEPPRA XR should be discontinued immediately if a serious hypersensitivity reaction is suspected [see Warnings and Precautions (5.6)].

Dosing and Administration

Patients should be instructed to only take KEPPRA XR once daily and to swallow the tablets whole. They should not be chewed, broken, or crushed.

Inform patients that they should not be concerned if they occasionally notice something that looks like swollen pieces of the original tablet in their stool.

Withdrawal of KEPPRA

Advise patients and caregivers not to discontinue use of KEPPRA XR without consulting with their healthcare provider. KEPPRA XR should normally be gradually withdrawn to reduce the potential of increased seizure frequency and status epilepticus [see Warnings and Precautions (5.8)].

Pregnancy

Advise patients to notify their healthcare provider if they become pregnant or intend to become pregnant during KEPPRA therapy. Encourage patients to enroll in the North American Antiepileptic Drug (NAAED) pregnancy registry if they become pregnant [see Use in Specific Populations (8.1)].

KEPPRA XR manufactured for
UCB, Inc.
Smyrna, GA 30080

KEPPRA XR is a registered trademark of the UCB Group of companies
© 2024, UCB, Inc., Smyrna, GA 30080
All rights reserved.

MEDICATION GUIDE
KEPPRA XR®(KEPP-ruh XR)(levetiracetam)
extended-release tablets, for oral use

Read this Medication Guide before you start taking KEPPRA XR and each time you get a refill. There may be new information. This information does not take the place of talking to your healthcare provider about your medical condition or treatment.

What is the most important information I should know about KEPPRA XR?

Like other antiepileptic drugs, KEPPRA XR may cause suicidal thoughts or actions in a very small number of people, about 1 in 500 people taking it.

Call a healthcare provider right away if you have any of these symptoms, especially if they are new, worse, or worry you:

- thoughts about suicide or dying
- attempts to commit suicide
- new or worse depression
- new or worse anxiety
- feeling agitated or restless
- panic attacks
- trouble sleeping (insomnia)
- new or worse irritability
- acting aggressive, being angry, or violent
- acting on dangerous impulses
- an extreme increase in activity and talking (mania)
- other unusual changes in behavior or mood

Do not stop KEPPRA XR without first talking to a healthcare provider.

- Stopping KEPPRA XR suddenly can cause serious problems. Stopping a seizure medicine suddenly can cause seizures that will not stop (status epilepticus).
- Suicidal thoughts or actions can be caused by things other than medicines. If you have suicidal thoughts or actions, your healthcare provider may check for other causes.

How can I watch for early symptoms of suicidal thoughts and actions?

- Pay attention to any changes, especially sudden changes, in mood, behaviors, thoughts, or feelings.
- Keep all follow-up visits with your healthcare provider as scheduled.

Call your healthcare provider between visits as needed, especially if you are worried about symptoms.

What is KEPPRA XR?

KEPPRA XR is a prescription medicine taken by mouth that is used to treat partial-onset seizures in people 12 years of age and older.

It is not known if KEPPRA XR is safe or effective in people under 12 years of age.

Before taking your medicine, make sure you have received the correct medicine. Compare the name above with the name on your bottle and the appearance of your medicine with the description of KEPPRA XR provided below. Tell your pharmacist immediately if you think you have been given the wrong medicine.

Who should not take KEPPRA XR?Do not take KEPPRA XR if you are allergic to levetiracetam.

What should I tell my healthcare provider before starting KEPPRA XR?

Before taking KEPPRA XR, tell your healthcare provider about all of your medical conditions, including if you:

- have or have had depression, mood problems or suicidal thoughts or behavior.
- have kidney problems.
- are pregnant or planning to become pregnant. It is not known if KEPPRA XR will harm your unborn baby. You and your healthcare provider will have to decide if you should take KEPPRA XR while you are pregnant. If you become pregnant while taking KEPPRA XR, talk to your healthcare provider about registering with the North American Antiepileptic Drug Pregnancy Registry. You can enroll in this registry by calling 1-888-233-2334 or go to http://www.aedpregnancyregistry.org. The purpose of this registry is to collect information about the safety of KEPPRA XR and other antiepileptic medicine during pregnancy.
- are breastfeeding or plan to breastfeed. KEPPRA XR can pass into your breast milk. It is not known if the KEPPRA XR that passes into your breast milk can harm your baby. Talk to your doctor about the best way to feed your baby while you receive KEPPRA.

Tell your healthcare provider about all the medicines you take, including prescription and over-the counter medicines, vitamins, and herbal supplements. Do not start a new medicine without first talking with your healthcare provider.
Know the medicines you take. Keep a list of them to show your healthcare provider and pharmacist each time you get a new medicine.

How should I take KEPPRA XR?

- Take KEPPRA XR exactly as your healthcare provider tells you to take it.
- Your healthcare provider will tell you how much KEPPRA XR to take and when to take it. KEPPRA XR is usually taken 1 time each day.
- Your healthcare provider may change your dose. Do notchange your dose without talking to your healthcare provider.
- Take KEPPRA XR with or without food.
- Swallow the tablets whole. Do notchew, break, or crush tablets.
- The inactive part of KEPPRA XR tablets may not dissolve after all the medicine has been released in your body. You may sometimes notice something in your bowel movement that looks like swollen pieces of the original tablet. This is normal.
- If you take too much KEPPRA XR, call your local Poison Control Center or go to the nearest emergency room right away.

What should I avoid while taking KEPPRA XR?

Do not drive, operate machinery or do other dangerous activities until you know how KEPPRA XR affects you. KEPPRA XR may make you dizzy or sleepy.

What are the possible side effects of KEPPRA XR?

KEPPRA XR can cause serious side effects including:

- See " What is the most important information I should know about KEPPRA XR?"

Call your healthcare provider right away if you have any of these symptoms:

- mood and behavior changes such as aggression, agitation, anger, anxiety, apathy, mood swings, depression, hostility, and irritability. A few people may get psychotic symptoms such as hallucinations (seeing or hearing things that are really not there), delusions (false or strange thoughts or beliefs) and unusual behavior.
- extreme sleepiness, tiredness, and weakness.
- allergic reactions such as swelling of the face, lips, eyes, tongue, and throat, trouble swallowing or breathing, and hives.
- a skin rash. Serious skin rashes can happen after you start taking KEPPRA XR. There is no way to tell if a mild rash will become a serious reaction.
- a serious allergic reaction that may affect your skin or other parts of your body such as your liver, kidneys, heart, or blood cells. This allergic reaction can be life-threatening and can cause death, particularly if it is not treated as early as possible. Call your healthcare provider right away if you have:

- a skin rash
- swelling of your face
- dark urine

- fever or swollen glands that do not go away
- shortness of breath
- yellowing of the skin or whites of the eyes

- problems with muscle coordination (problems walking and moving).

The most common side effects seen in people who take KEPPRA XR include:

- sleepiness

- irritability

Tell your healthcare provider if you have any side effect that bothers you or that does not go away.

These are not all the possible side effects of KEPPRA XR. For more information, ask your healthcare provider or pharmacist.

Call your doctor for medical advice about side effects. You may report side effects to FDA at 1-800-FDA-1088.

How should I store KEPPRA XR?

- Store KEPPRA XRat room temperature, between 59°F to 86°F (15°C to 30°C) away from heat and light.
- Keep KEPPRA XR and all medicines out of the reach of children.

General information about the safe and effective use of KEPPRA XR.

Medicines are sometimes prescribed for purposes other than those listed in a Medication Guide. Do not use KEPPRA XR for a condition for which it was not prescribed. Do not give KEPPRA XR to other people, even if they have the same symptoms that you have. It may harm them. You can ask your pharmacist or healthcare provider for information about KEPPRA XR that is written for health professionals.

What are the ingredients in KEPPRA XR?

KEPPRA XR tabletactive ingredient :levetiracetam

Inactive ingredients: colloidal anhydrous silica, hypromellose, magnesium stearate, polyethylene glycol 6000, polyvinyl alcohol-partially hydrolyzed, titanium dioxide (E171), Macrogol/PEG3350, and talc. The imprinting ink contains shellac, FD&C Red #40, n-butyl alcohol, propylene glycol, titanium dioxide, ethanol, and methanol. KEPPRA XR does not contain lactose or gluten.

Distributed by
UCB, Inc.
Smyrna, GA 30080

KEPPRA XR is a registered trademark of the UCB Group of companies
© 2024, UCB, Inc., Smyrna, GA 30080
All rights reserved.

For more information, go to www.keppraxr.com or call 1- (844) 599-CARE (2273).

This Medication Guide has been approved by the U.S. Food and Drug Administration.

Revised: 3/2024

PRINCIPAL DISPLAY PANEL - 500 mg Tablet Bottle Label

NDC 50474-598-66
60 tablets

Once Daily Dosing

KEPPRA
XR®(levetiracetam)
extended-release tablets

500 mg tablets

Dispense accompanying
Medication Guide to
each patient.

Rx only

PRINCIPAL DISPLAY PANEL - 750 mg Tablet Bottle Label

NDC 50474-599-66
60 tablets

Once Daily Dosing

KEPPRA
XR®(levetiracetam)
extended-release tablets

750 mg tablets

Dispense accompanying
Medication Guide to each patient.

Rx only